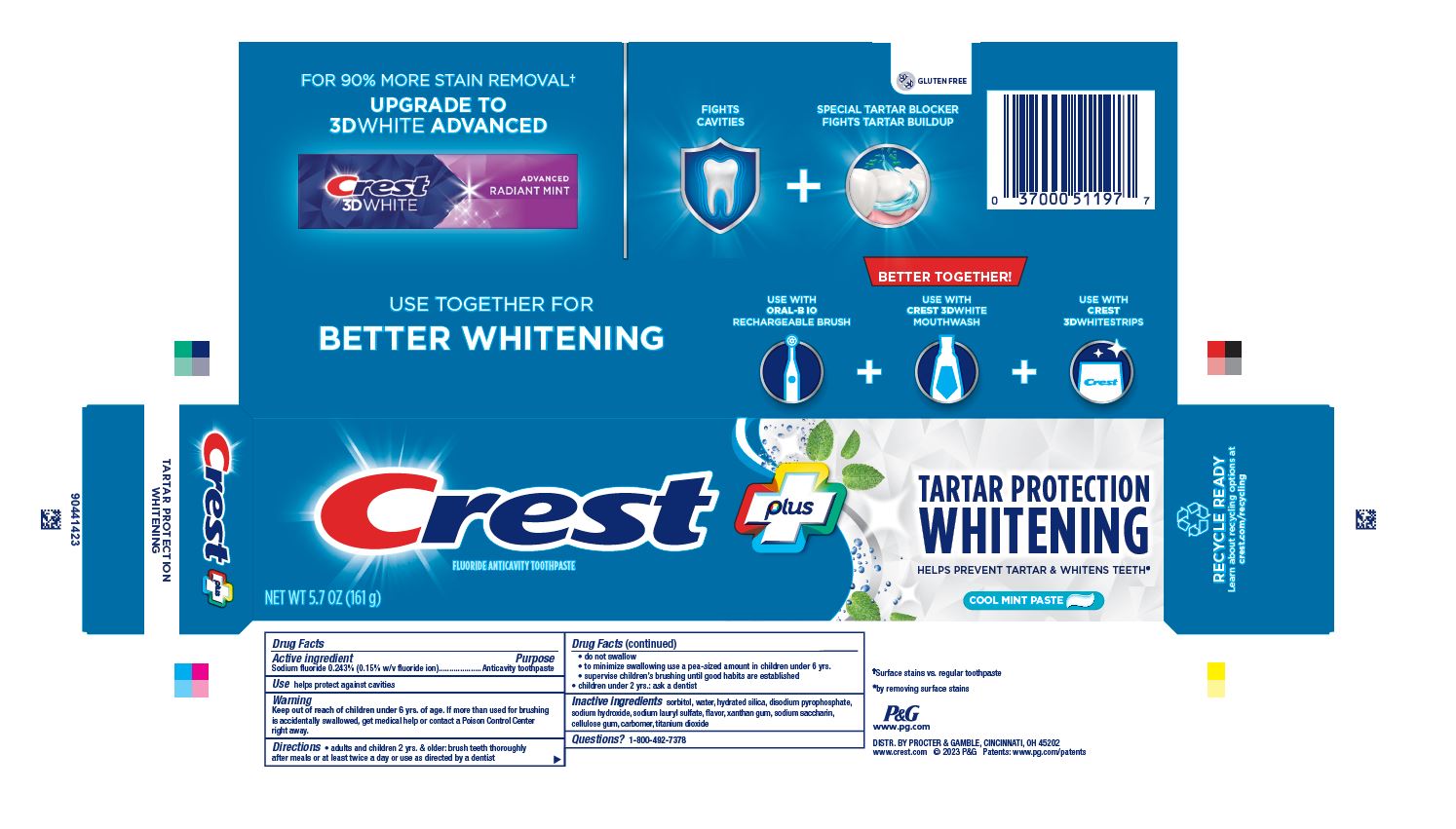 DRUG LABEL: Crest plus
NDC: 69423-818 | Form: PASTE, DENTIFRICE
Manufacturer: The Procter & Gamble Manufacturing Company
Category: otc | Type: HUMAN OTC DRUG LABEL
Date: 20250821

ACTIVE INGREDIENTS: SODIUM FLUORIDE 1.5 mg/1 g
INACTIVE INGREDIENTS: CARBOXYPOLYMETHYLENE; CARBOXYMETHYLCELLULOSE SODIUM, UNSPECIFIED FORM; HYDRATED SILICA; WATER; SODIUM ACID PYROPHOSPHATE; SORBITOL; SODIUM HYDROXIDE; SODIUM LAURYL SULFATE; SACCHARIN SODIUM; XANTHAN GUM; TITANIUM DIOXIDE

Crest plus Tartar Protection Whitening Cool Mint Paste

Drug Facts

Active ingredient

Sodium fluoride 0.243%

Purpose

Anticavity toothpaste

Use

helps protect against cavities

Warning

Keep out of reach of children under 6 yrs. of age.If more than used for brushing is accidentally swallowed, get medical help or contact a Poison Control Center right away.

Directions

- adults and children 2 yrs. & older: brush teeth thoroughly after meals or at least twice a day or use as directed by a dentist
  - do not swallow
  - to minimize swallowing use a pea-sized amount in children under 6
  - supervise children's brushing until good habits are established
- children under 2 yrs.: ask a dentist

Inactive ingredients

sorbitol, water, hydrated silica, disodium pyrophosphate,
sodium hydroxide, sodium lauryl sulfate, flavor, xanthan gum, sodium saccharin,
cellulose gum, carbomer, titanium dioxide

Questions?

1-800-492-7378

Dist. by Procter & Gamble, Cincinnati, OH 45202

PRINCIPAL DISPLAY PANEL - 161 g Tube Carton

Crest plus

FLOURIDE ANTICAVITY TOOTHPASTE

NET WT 5.7 OZ (161 G)

TARTA PROTECTION

WHITENING

HELPS PREVENT TARTAR & WHITENS TEETH

COOL MINT PASTE